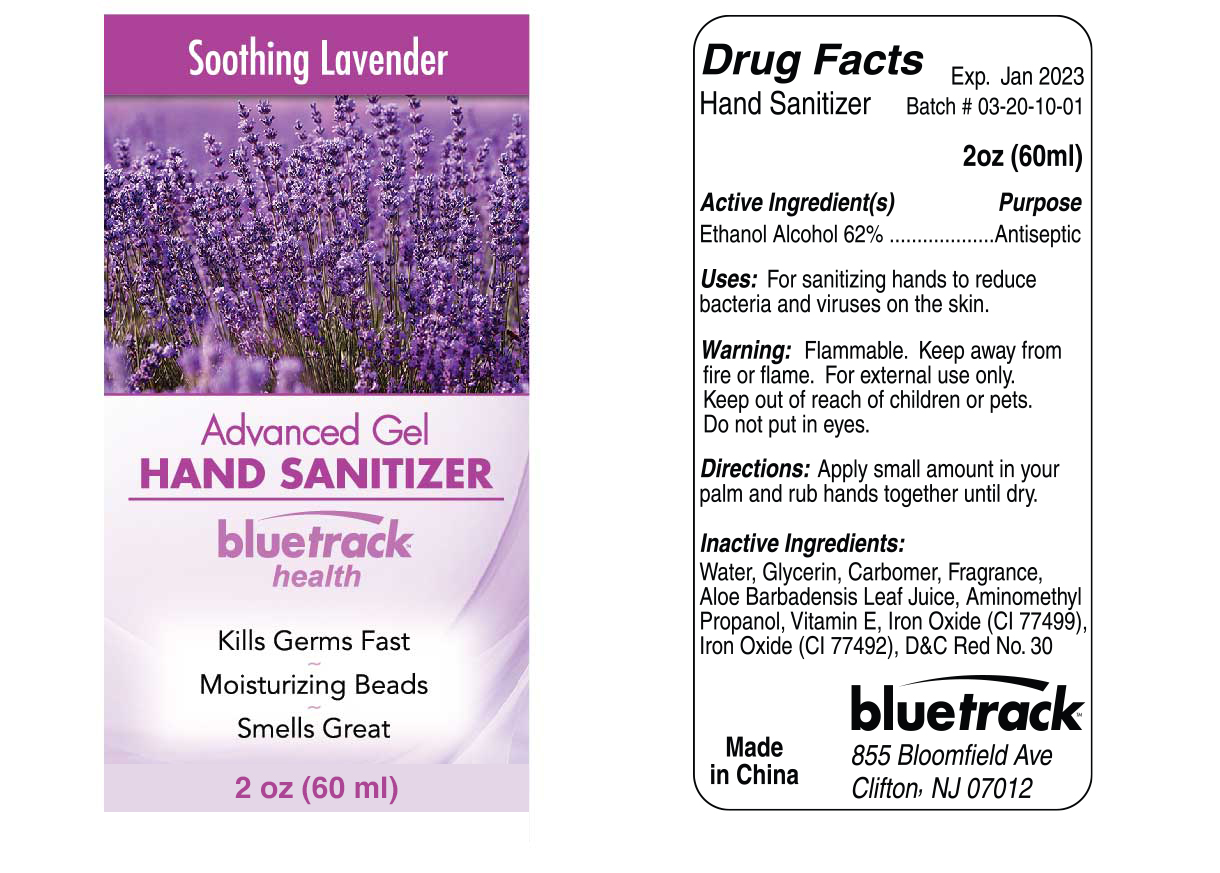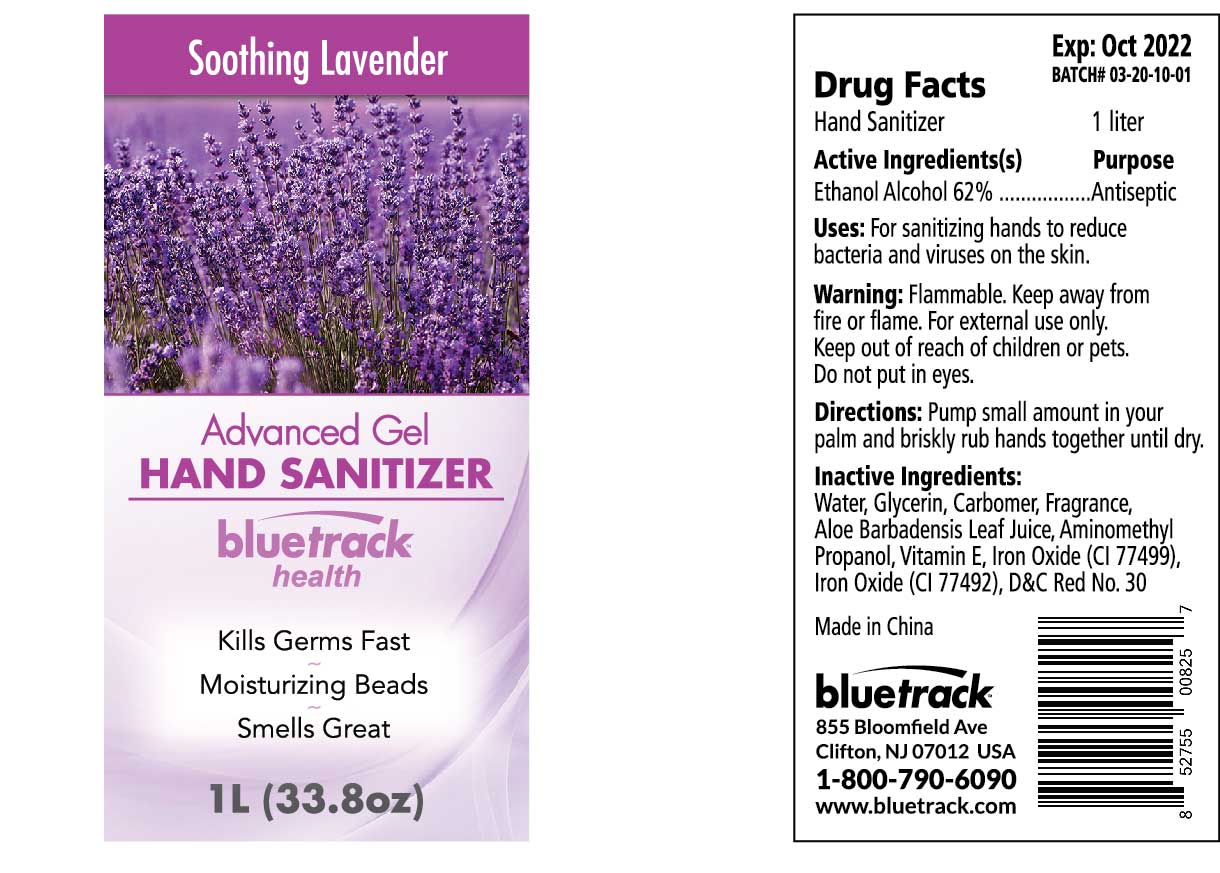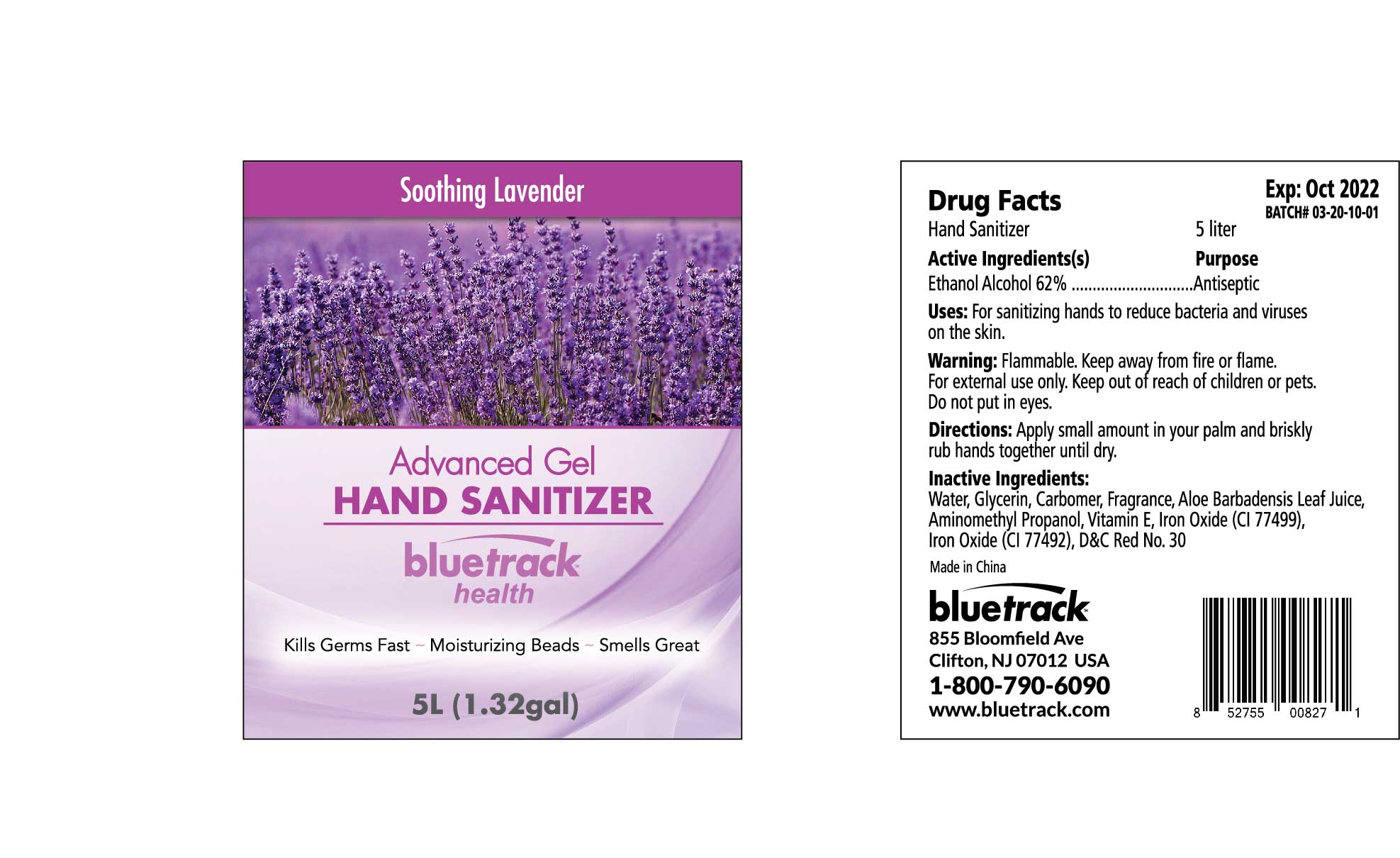 DRUG LABEL: Advanced Gel Hand Sanitizer soothing Lavender
NDC: 81209-200 | Form: GEL
Manufacturer: BLUETRACK INC
Category: otc | Type: HUMAN OTC DRUG LABEL
Date: 20210821

ACTIVE INGREDIENTS: ALCOHOL 62 mL/100 mL
INACTIVE INGREDIENTS: D&C RED NO. 30; ALOE VERA LEAF; FERRIC OXIDE YELLOW; AMINOMETHYLPROPANOL; TOCOPHEROL; FERROSOFERRIC OXIDE; GLYCERIN; CARBOMER 940; WATER; FRAGRANCE LAVENDER ORC1800979

Advanced Gel HAND SANITIZER Soothing Lavender

Active Ingredient(s)

Ethanol Alcohol 62% w/v. Purpose: Antiseptic

Purpose

Antiseptic, Advanced Hand Sanitizer Soothing Lavender

Use

For Sanitizing hands to reduce bacteria and virus on the skin

Warnings

Flammable. Keep away from fire or flame

For external use only.

Keep out of reach of children or pets.

WHEN USING

Do not put in eyes

Directions

Apply Small amount in your palm and briskly rub hands together until dry.

Inactive ingredients

Inactive Ingredients:Water, Glycerin, Carbomer, Fragrance, Aloe Barbadensis Leaf Juice, Aminomethyl Propanol, Vitamin E, Iron Oxide(CI 77499),Iron Oxide(CI 77492), D&C Red No.30.

Package Label - Principal Display Panel

60mL NDC : 81209-200-03

5000 mL NDC: 81209-200-01

1000mL NDC: 81209-200-02